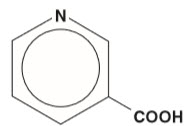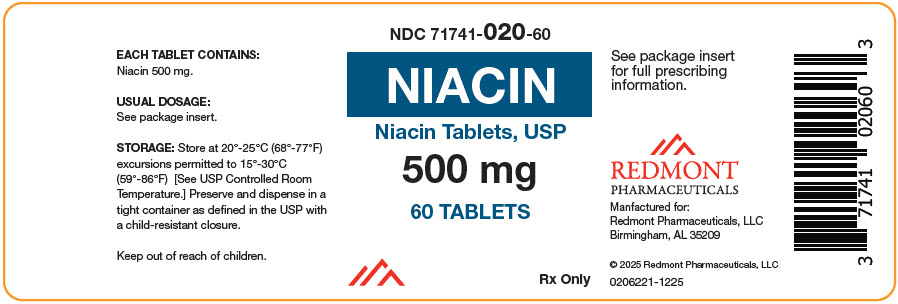 DRUG LABEL: Niacin
NDC: 71741-020 | Form: TABLET
Manufacturer: Redmont Pharmaceuticals, LLC
Category: prescription | Type: HUMAN PRESCRIPTION DRUG LABEL
Date: 20251217

ACTIVE INGREDIENTS: Niacin 500 mg/1 1
INACTIVE INGREDIENTS: CROSCARMELLOSE SODIUM; HYDROGENATED SOYBEAN OIL; MAGNESIUM STEARATE; MICROCRYSTALLINE CELLULOSE

Niacin Tablets, USP
500 mg

DESCRIPTION

Niacin or nicotinic acid, a water-soluble B-complex vitamin and antihyperlipidemic agent, is 3-pyridinecarboxylic acid. It is a white, crystalline powder, sparingly soluble in water. It has the following structural formula:

MW=123.11 |  | C6H5NO2

Each Niacin Tablet, for oral administration, contains 500 mg of nicotinic acid. In addition, each tablet contains the following inactive ingredients: croscarmellose sodium, hydrogenated vegetable oil, magnesium stearate and microcrystalline cellulose.

CLINICAL PHARMACOLOGY

The role of low-density lipoprotein (LDL) cholesterol in atherogenesis is supported by pathological observations, clinical studies, and many animal experiments. Observational epidemiological studies have clearly established that high total or LDL cholesterol and low high-density lipoprotein (HDL) cholesterol are risk factors for coronary heart disease. The Coronary Drug Project^1, completed in 1975, was designed to assess the safety and efficacy of nicotinic acid and other lipid-altering drugs in men 30 to 64 years old with a history of myocardial infarction (MI). Over an observation period of five years, nicotinic acid showed a statistically significant benefit in decreasing nonfatal, recurrent myocardial infarctions. The incidence of definite, nonfatal MI was 8.9% for the 1,119 patients randomized to nicotinic acid versus 12.2% for the 2,789 patients who received placebo (p< 0.004). Though total mortality was similar in the two groups at five years (24.4% with nicotinic acid versus 25.4% with placebo; p = N.S.), in a fifteen year cumulative follow-up there were 11% (69) fewer deaths in the nicotinic acid group compared to the placebo cohort (52.0% versus 58.2%; p= 0.0004)^2.

The Cholesterol-Lowering Atherosclerosis Study (CLAS) was a randomized, placebo-controlled, angiographic trial testing combined colestipol and nicotinic acid therapy in 162 non-smoking males with previous coronary bypass surgery^3. The primary, per subject cardiac endpoint was global coronary artery change score. After two years, 61% of patients in the placebo cohort showed disease progression by global change score (N=82), compared with only 38.8% of drug-treated subjects (N=80), when both native arteries and grafts were considered (p<0.005). In a follow-up to this trial in a subgroup of 103 patients treated for four years, again, significantly fewer patients in the drug-treated group demonstrated progression than in the placebo cohort (48% versus 85%, respectively; p< 0.0001)^4.

The Familial Atherosclerosis Treatment Study (FATS) in 146 men ages 62 and younger with apolipoprotein B levels ≥125 mg/dL, established coronary artery disease, and family histories of vascular disease, assessed change in severity of disease in the proximal coronary arteries by quantitative arteriography^5. Patients were given dietary counseling and randomized to treatment with either conventional therapy with double placebo (or placebo plus colestipol if the LDL cholesterol was elevated); lovastatin plus colestipol; or nicotinic acid plus colestipol. In the conventional therapy group, 46% of patients had disease progression (and no regression) in at least one of nine proximal coronary segments. In contrast, progression (as the only change) was seen in only 25% in the nicotinic acid plus colestipol group. Though not an original endpoint of the trial, clinical events (death, myocardial infarction, or revascularization for worsening angina) occurred in 10 of 52 patients who received conventional therapy, compared with 2 of 48 who received nicotinic acid plus colestipol.

Nicotinic acid (but not nicotinamide) in gram doses produces an average 10% to 20% reduction in total and LDL cholesterol, a 30% to 70% reduction in triglycerides, and an average 20% to 35% increase in HDL cholesterol. The magnitude of individual lipid and lipoprotein responses may be influenced by the severity and type of underlying lipid abnormality. The increase in total HDL is associated with a shift in the distribution of HDL sub-fractions (as defined by ultra-centrifugation) with an increase in the HDL2:HDL3 ratio and an increase in apolipoprotein A-I content. The mechanism by which nicotinic acid exerts these effects is not entirely understood, but may involve several actions, including a decrease in esterification of hepatic triglycerides. Nicotinic acid treatment also decreases the serum levels of apolipoprotein B-100 (apo B), the major protein component of the very low-density lipoprotein (VLDL) and LDL fractions, and of lipoprotein a [Lp(a)], a variant form of LDL independently associated with coronary risk. The effect of nicotinic acid-induced changes in lipids/lipoproteins on cardiovascular morbidity or mortality in individuals without pre-existing coronary disease has not been established.

Pharmacokinetics

Following an oral dose, the pharmacokinetic profile of nicotinic acid is characterized by rapid absorption from the gastrointestinal tract and a short plasma elimination half-life. At a 1 gram dose, peak plasma concentrations of 15 to 30 µg/mL are reached within 30 to 60 minutes. Approximately 88% of an oral pharmacologic dose is eliminated by the kidneys as unchanged drug and nicotinuric acid, its primary metabolite. The plasma elimination half-life of nicotinic acid ranges from 20 to 45 minutes.

INDICATIONS AND USAGE

I. Therapy with lipid-altering agents should be only one component of multiple risk factor intervention in those individuals at significantly increased risk for atherosclerotic vascular disease due to hypercholesterolemia. Nicotinic acid, alone or in combination with a bile-acid binding resin, is indicated as an adjunct to diet for the reduction of elevated total and LDL cholesterol levels in patients with primary hypercholesterolemia (Types IIa and IIb)†, when the response to a diet restricted in saturated fat and cholesterol and other nonpharmacologic measures alone has been inadequate (see also the NCEP treatment guidelines^6). Prior to initiating therapy with nicotinic acid, secondary causes for hypercholesterolemia (e.g., poorly controlled diabetes mellitus, hypothyroidism, nephrotic syndrome, dysproteinemias, obstructive liver disease, other drug therapy, alcoholism) should be excluded, and a lipid profile performed to measure total cholesterol, HDL cholesterol, and triglycerides.

II. Nicotinic acid is also indicated as adjunctive therapy for the treatment of adult patients with very high serum triglyceride levels (Types IV and V hyperlipidemia)† who present a risk of pancreatitis and who do not respond adequately to a determined dietary effort to control them. Such patients typically have serum triglyceride levels over 2,000 mg/dL and have elevations of VLDL cholesterol as well as fasting chylomicrons (Type V hyperlipidemia)†. Subjects who consistently have total serum or plasma triglycerides below 1,000 mg/dL are unlikely to develop pancreatitis. Therapy with nicotinic acid may be considered for those subjects with triglyceride elevations between 1,000 and 2,000 mg/dL who have a history of pancreatitis or of recurrent abdominal pain typical of pancreatitis. Some Type IV patients with triglycerides under 1,000 mg/dL may, through dietary or alcoholic indiscretion, convert to a Type V pattern with massive triglyceride elevations accompanying fasting chylomicronemia, but the influence of nicotinic acid therapy on the risk of pancreatitis in such situations has not been adequately studied. Drug therapy is not indicated for patients with Type I hyperlipoproteinemia, who have elevations of chylomicrons and plasma triglycerides, but who have normal levels of VLDL. Inspection of plasma refrigerated for 14 hours is helpful in distinguishing Types I, IV, and V hyperlipoproteinemia^7.

† Classification of Hyperlipoproteinemias
 | Lipoproteins | Lipid Elevations
Type | Elevated | Major | Minor
I (rare) | Chylomicrons | TG | ↑→ C
IIa | LDL | C | .....
IIb | LDL, VLDL | C | TG
III (rare) | IDL | C/TG | .....
IV | VLDL | TG | ↑→ C
V (rare) | Chylomicrons, VLDL | TG | ↑→ C
C = cholesterol, TG = triglycerides
LDL = low-density lipoprotein
VLDL = very low-density lipoprotein
IDL = intermediate-density lipoprotein

CONTRAINDICATIONS

Nicotinic acid is contraindicated in patients with a known hypersensitivity to any component of this medication; significant or unexplained hepatic dysfunction; active peptic ulcer disease; or arterial bleeding.

WARNINGS

Liver Dysfunction

Cases of severe hepatic toxicity, including fulminant hepatic necrosis have occurred in patients who have substituted sustained-release (modified-release, timed-release) nicotinic acid products for immediate-release (crystalline) nicotinic acid at equivalent doses.

Liver function tests should be performed on all patients during therapy with nicotinic acid. Serum transaminase levels, including ALT (SGPT), should be monitored before treatment begins, every six weeks to twelve weeks for the first year, and periodically thereafter (e.g., at approximately 6 month intervals). Special attention should be paid to patients who develop elevated serum transaminase levels, and in these patients, measurements should be repeated promptly and then performed more frequently. If the transaminase levels show evidence of progression, particularly if they rise to three times the upper limit of normal and are persistent, the drug should be discontinued. Liver biopsy should be considered if elevations persist beyond discontinuation of the drug.

Nicotinic acid should be used with caution in patients who consume substantial quantities of alcohol and/or have a past history of liver disease. Active liver diseases or unexplained transaminase elevations are contraindications to the use of nicotinic acid.

Skeletal Muscle

Rare cases of rhabdomyolysis have been associated with concomitant administration of lipid-altering doses (≥1 g/day) of nicotinic acid and HMG-CoA reductase inhibitors. Physicians contemplating combined therapy with HMG-CoA reductase inhibitors and nicotinic acid should carefully weigh the potential benefits and risks and should carefully monitor patients for any signs and symptoms of muscle pain, tenderness, or weakness, particularly during the initial months of therapy and during any periods of upward dosage titration of either drug. Periodic serum creatine phosphokinase (CPK) and potassium determinations should be considered in such situations, but there is no assurance that such monitoring will prevent the occurrence of severe myopathy.

PRECAUTIONS

General

Before instituting therapy with nicotinic acid, an attempt should be made to control hyperlipidemia with appropriate diet, exercise, and weight reduction in obese patients, and to treat other underlying medical problems [see INDICATIONS AND USAGE ].

Patients with a past history of jaundice, hepatobiliary disease, or peptic ulcer should be observed closely during nicotinic acid therapy. Frequent monitoring of liver function tests and blood glucose should be performed to ascertain that the drug is producing no adverse effects on these organ systems. Diabetic patients may experience a dose-related rise in glucose intolerance, the clinical significance of which is unclear. Diabetic or potentially diabetic patients should be observed closely. Adjustment of diet and/or hypoglycemic therapy may be necessary.

Caution should also be used when nicotinic acid is used in patients with unstable angina or in the acute phase of myocardial infarction, particularly when such patients are also receiving vasoactive drugs such as nitrates, calcium channel blockers, or adrenergic blocking agents.

Elevated uric acid levels have occurred with nicotinic acid therapy, therefore use with caution in patients predisposed to gout.

Drug Interactions

HMG‑CoA Reductase Inhibitors

See WARNINGS, Skeletal Muscle.

Antihypertensive Therapy

Nicotinic acid may potentiate the effects of ganglionic blocking agents and vasoactive drugs resulting in postural hypotension.

Aspirin

Concomitant aspirin may decrease the metabolic clearance of nicotinic acid. The clinical relevance of this finding is unclear.

Other

Concomitant alcohol or hot drinks may increase the side effects of flushing and pruritus and should be avoided at the time of drug ingestion.

Carcinogenesis, Mutagenesis, Impairment of Fertility

Nicotinic acid administered to mice for a lifetime as a 1% solution in drinking water was not carcinogenic. The mice in this study received approximately 6 to 8 times a human dose of 3,000 milligrams/day as determined on a milligram/square meter basis. Nicotinic acid was negative for mutagenicity in the Ames test. No studies on impairment of fertility have been performed.

Pregnancy

Animal reproduction studies have not been conducted with nicotinic acid. It is also not known whether nicotinic acid at doses typically used for lipid disorders can cause fetal harm when administered to pregnant women or whether it can affect reproductive capacity. If a woman receiving nicotinic acid for primary hypercholesterolemia (Types IIa or IIb) becomes pregnant, the drug should be discontinued. If a woman being treated with nicotinic acid for hypertriglyceridemia (Types IV or V) conceives, the benefits and risks of continued drug therapy should be assessed on an individual basis.

Nursing Mothers

It is not known whether this drug is excreted in human milk. Because many drugs are excreted in human milk and because of the potential for serious adverse reactions in nursing infants from lipid-altering doses of nicotinic acid, a decision should be made whether to discontinue nursing or to discontinue the drug, taking into account the importance of the drug to the mother.

Pediatric Use

Safety and effectiveness in children and adolescents have not been established.

ADVERSE REACTIONS

Cardiovascular: Atrial fibrillation and other cardiac arrhythmias, orthostasis, hypotension.

Gastrointestinal: Dyspepsia, vomiting, diarrhea, peptic ulceration, jaundice, abnormal liver function tests.

Skin: Mild to severe cutaneous flushing, pruritus, hyperpigmentation, acanthosis nigricans, dry skin.

Metabolic: Decreased glucose tolerance, hyperuricemia, gout.

Eye: Toxic amblyopia, cystoid macular edema.

Nervous System / Psychiatric: Headache.

OVERDOSAGE

Supportive measures should be undertaken in the event of an overdose.

DOSAGE AND ADMINISTRATION

The usual adult dosage of nicotinic acid is 1 to 2 grams two or three times a day. Doses should be individualized according to the patient's response. Start with one-half tablet (250 mg) as a single daily dose following the evening meal. The frequency of dosing and total daily dose can be increased every four to seven days until the desired LDL cholesterol and/or triglyceride level is achieved or the first-level therapeutic dose of 1.5 to 2 grams/day is reached. If the patient's hyperlipidemia is not adequately controlled after 2 months at this level, the dosage can then be increased at two to four week intervals to 3 grams/day (1 gram three times per day). In patients with marked lipid abnormalities, a higher dose is occasionally required, but generally should not exceed 6 grams/day.

Flushing of the skin appears frequently and can be minimized by pretreatment with aspirin or non-steroidal anti-inflammatory drugs. Tolerance to this flushing develops rapidly over the course of several weeks. Flushing, pruritus, and gastrointestinal distress are also greatly reduced by slowly increasing the dose of nicotinic acid and avoiding administration on an empty stomach.

Sustained-release (modified-release, timed-release) nicotinic acid preparations should not be substituted for equivalent doses of immediate-release (crystalline) nicotinic acid.

HOW SUPPLIED

Niacin Tablets, USP 500 mg.

Each tablet is a white, capsule-shaped, scored, uncoated tablet, debossed "A2" to the left and "01" to the right of the score, with "A" on the unscored side.

Niacin is available in bottles of 30 tablets (NDC 71741-020-30), 60 tablets (NDC 71741-020-60) and 90 tablets (NDC 71741-020-90).

Dispense in a tight container as defined in the USP with a child-resistant closure.

STORAGE AND HANDLING

Store at 20° to 25°C (68° to 77°F); excursions permitted to 15° to 30°C (59° to 86°F) [See USP Controlled Room Temperature].

REFERENCES

1. The Coronary Drug Project Research Group. Clofibrate and Niacin in Coronary Heart Disease. JAMA 1975; 231:360–81.
2. Canner PL et al. Fifteen Year Mortality in Coronary Drug Project Patients: Long-Term Benefit with Niacin. JACC 1986; 8(6):1245–55.
3. Blankenhorn DH et al. Beneficial Effects of Combined Colestipol-Niacin Therapy on Coronary Atherosclerosis and Coronary Venous Bypass Grafts. JAMA 1987; 257(23):3233–40.
4. Cashin-Hemphill et al. Beneficial Effects of Colestipol-Niacin on Coronary Atherosclerosis. JAMA 1990; 264(23):3013–17.
5. Brown G et al. Regression of Coronary Artery Disease as a Result of Intensive Lipid-Lowering Therapy in Men with High Levels of Apolipoprotein B. NEJM 1990; 323:1289–98.
6. Report of the National Cholesterol Education Program Expert Panel on Detection, Evaluation, and Treatment of High Blood Cholesterol. Arch Int Med 1988; 148:36–69.
7. Nikkila EA: Familial lipoprotein lipase deficiency and related disorders of chylomicron metabolism. In Stanbury JB et al. (eds.): The Metabolic Basis of Inherited Disease, 5th ed., McGraw-Hill, 1983, Chap. 30, pp. 622– 642.

Manufactured for
Redmont Pharmaceuticals, LLC
Birmingham, AL 35209

020111
Revised 0620

© 2020 Redmont Pharmaceuticals, LLC

PRINCIPAL DISPLAY PANEL - 500 mg Tablet Bottle Label

NDC 71741-020-60

NIACIN
Niacin Tablets, USP

500 mg

60 TABLETS
Rx only